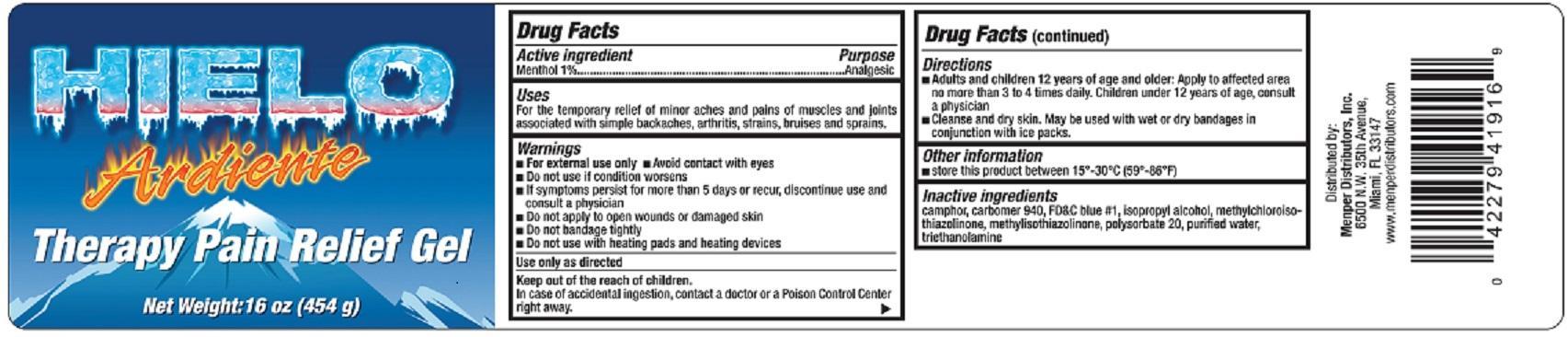 DRUG LABEL: Hielo Ardiente
NDC: 53145-002 | Form: GEL
Manufacturer: Menper Distributors, Inc.
Category: otc | Type: HUMAN OTC DRUG LABEL
Date: 20250722

ACTIVE INGREDIENTS: MENTHOL 1 g/100 g
INACTIVE INGREDIENTS: CAMPHOR (SYNTHETIC); CARBOMER 940; FD&C BLUE NO. 1; ISOPROPYL ALCOHOL; METHYLCHLOROISOTHIAZOLINONE; METHYLISOTHIAZOLINONE; POLYSORBATE 20; WATER; TRIETHANOLAMINE BENZOATE

Hielo Ardiente

Active ingredient

Menthol 1%

Purpose

Analgesic

Uses

For the temporary relief of minor aches and pains of muscles and joints associated with simple backaches, arthritis, strains, bruises and sprains.

Warnings

For external use only

- Avoid contact with eyes
- Do not use if condition worsens
- If symptoms persist for more than 5 days or recur, discontinue use and consult a physician
- Do not apply to open wounds or damaged skin
- Do not bandage tightly
- Do not use with heating pads or heating devices

Use only as directed

Keep out of reach of children.

In case of accidental ingestion, contact a doctor or a Poison Control Center right away.

Directions

- Adults and children 12 years of age or older:Apply to affected area no more than 3 to 4 times daily. Children under 12 years of age, consult a physician
- Cleanse and dry skin. May be used with wet or dry bandages in conjuction with ice packs.

Inactive ingredients

camphor, carbomer 940, FD&C blue #1, isopropyl alcohol, methylchloroisothiazolinone, methylisothiazolinone, polysorbate 20, purified water, triethanolamine